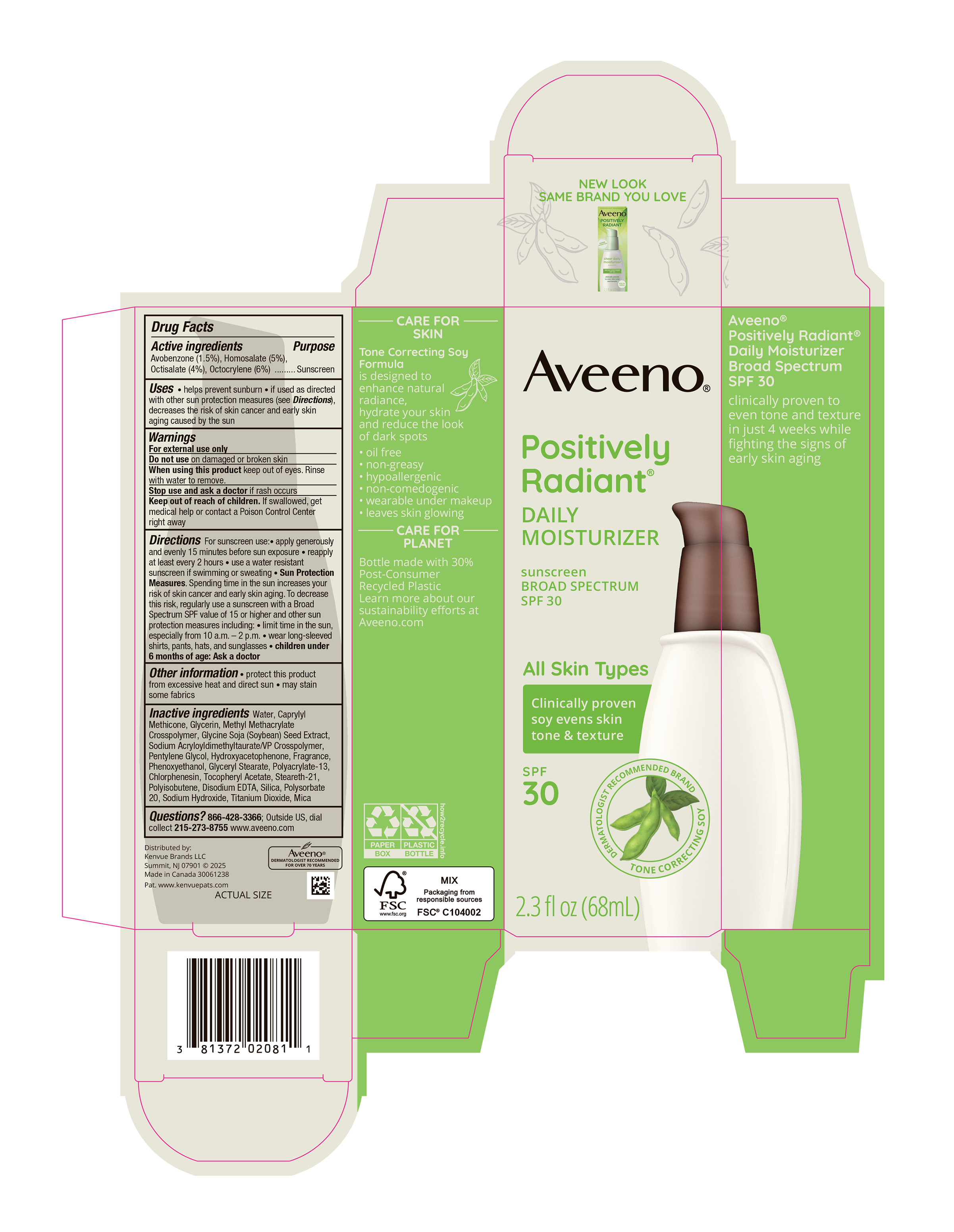 DRUG LABEL: Aveeno Positively Radiant Daily Moisturizer Sunscreen Broad Spectrum SPF 30
NDC: 69968-0765 | Form: LOTION
Manufacturer: Kenvue Brands LLC
Category: otc | Type: HUMAN OTC DRUG LABEL
Date: 20250805

ACTIVE INGREDIENTS: AVOBENZONE 15 mg/1 mL; HOMOSALATE 50 mg/1 mL; OCTISALATE 40 mg/1 mL; OCTOCRYLENE 60 mg/1 mL
INACTIVE INGREDIENTS: POLYACRYLATE-13; POLYSORBATE 20; SODIUM HYDROXIDE; TITANIUM DIOXIDE; MICA; GLYCERYL MONOSTEARATE; CHLORPHENESIN; SOYBEAN; METHYL METHACRYLATE/GLYCOL DIMETHACRYLATE CROSSPOLYMER; PENTYLENE GLYCOL; HYDROXYACETOPHENONE; PHENOXYETHANOL; .ALPHA.-TOCOPHEROL ACETATE, D-; WATER; CAPRYLYL TRISILOXANE; GLYCERIN; STEARETH-21; EDETATE DISODIUM ANHYDROUS; SILICON DIOXIDE

Aveeno Positively Radiant Daily Moisturizer Sunscreen Broad Spectrum SPF 30

Drug Facts

ACTIVE INGREDIENT

PURPOSE

Avobenzone (1.5%)…………………....…………………...Sunscreen

Homosalate (5%)…………………....……………………...Sunscreen

Octisalate (4%)…………………....……………………......Sunscreen

Octocrylene (6%) …………………....……………………..Sunscreen

Use

- helps prevent sunburn
- if used as directed with other sun protection measures (see Directions), decreases the risk of skin cancer an early skin aging caused by the sun

Warnings

- For external use only

- Do not use on damaged or broken skin

- When using this product keep out of eyes. Rinse with water to remove.

- Stop use and ask a doctor if rash occurs

- Keep out of reach of children. If swallowed, get medical help or contact a Poison Control Center right away

Directions

For sunscreen use:

- apply generously and evenly 15 minutes before sun exposure
- reapply at least every 2 hours
- use a water resistant sunscreen if swimming or sweating
- Sun Protection Measures. Spending time in the sun increases your risk of skin cancer and early skin aging. To decrease this risk, regularly use a sunscreen with a Broad Spectrum SPF value of 15 or higher and other sun protection measures including:
- limit time in the sun, especially from 10 a.m. – 2 p.m.
- wear long-sleeved shirts, pants, hats, and sunglasses
- children under 6 months of age: Ask a doctor

Other information

- protect the product from excessive heat and direct sun
- may stain some fabrics

Inactive ingredients

Water, Caprylyl Methicone, Glycerin, Methyl Methacrylate Crosspolymer, Glycine Soja (Soybean) Seed Extract, Sodium Acryloyldimethyltaurate/VP Crosspolymer, Pentylene Glycol, Hydroxyacetophenone, Fragrance, Phenoxyethanol, Glyceryl Stearate, Polyacrylate-13, Chlorphenesin, Tocopheryl Acetate, Steareth-21, Polyisobutene, Disodium EDTA, Silica, Polysorbate 20, Sodium Hydroxide, Titanium Dioxide, Mica

Questions?

866-428-3366; Outside US, dial collect 215-273-8755 www.aveeno.com

Distributed by:

Kenvue Brands LLC

Summit, NJ 07901

PRINCIPAL DISPLAY PANEL - 68 mL Bottle Carton

Aveeno®

Positively

Radiant®

DAILY

MOISTURIZER

sunscreen

BROAD SPECTRUM

SPF 30

All Skin Types

Clinically proven

soy evens skin

tone & texture

SPF

30

DERMATOLOGIST RECOMMENDED BRAND

TONE CORRECTING SOY

2.3 fl oz (68 mL)